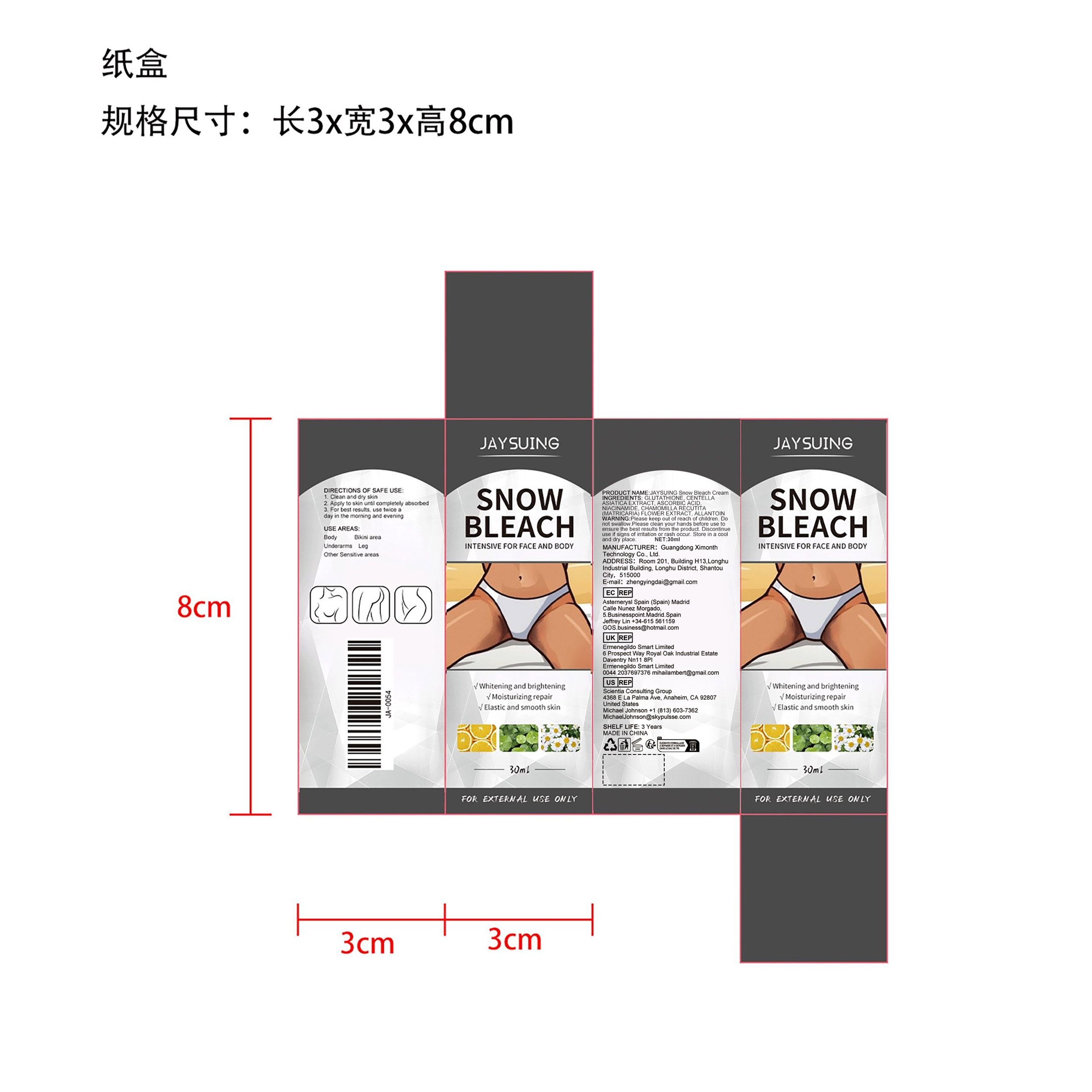 DRUG LABEL: JAYSUING Snow Bleach Cream
NDC: 84660-024 | Form: CREAM
Manufacturer: Guangdong Ximonth Technology Co., Ltd.
Category: otc | Type: HUMAN OTC DRUG LABEL
Date: 20240924

ACTIVE INGREDIENTS: CENTELLA ASIATICA TRITERPENOIDS 6 mg/30 mg; NIACINAMIDE 4.5 mg/30 mg; ASCORBIC ACID 4.5 mg/30 mg; GLUTATHIONE 3 mg/30 mg; CHAMOMILE 3 mg/30 mg
INACTIVE INGREDIENTS: ALLANTOIN 9 mg/30 mg

Active Ingredient(s)

GLUTATHIONE, CENTELLA ASIATICA EXTRACT,ASCORBIC ACID,NIACINAMIDE, CHAMOMILLA RECUTITA(MATRICARIA) FLOWER EXTRACT

Purpose

Elastic and smooth skin

Use

1. Clean and dry skin
2. Apply to skin until completely absorbed
3. For best results, use twice aday in the morning and evening

Warnings

Please keep out of reach of children.Do not swallow.Please clean your hands before use to ensure the best results from the product.Discontinue use if signs of irritation or rash occur.Store in a cool and dry place

Do not use

Discontinue use if signs of irritation or rash occur

STOP USE

Discontinue use if signs of irritation or rash occur

KEEP OUT OF REACH OF CHILDREN

Please keep out of reach of children. Do not swallow.

STORAGE AND HANDLING

Avoid freezing and excessive heat above 40C (104F) ）
Store in a cool and dry place.

INACTIVE INGREDIENT

ALLANTOIN